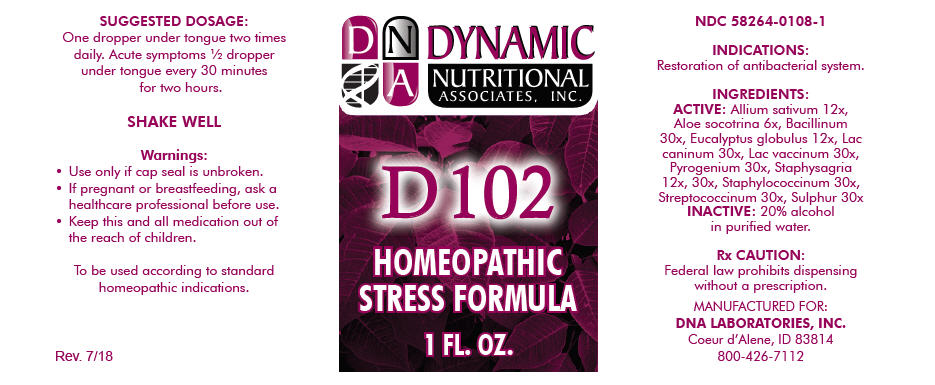 DRUG LABEL: D-102
NDC: 58264-0108 | Form: SOLUTION
Manufacturer: DNA Labs, Inc.
Category: homeopathic | Type: HUMAN OTC DRUG LABEL
Date: 20250113

ACTIVE INGREDIENTS: GARLIC 12 [hp_X]/1 mL; ALOE 6 [hp_X]/1 mL; MYCOBACTERIUM TUBERCULOSIS 30 [hp_X]/1 mL; EUCALYPTUS GLOBULUS LEAF 12 [hp_X]/1 mL; CANIS LUPUS FAMILIARIS MILK 30 [hp_X]/1 mL; COW MILK 30 [hp_X]/1 mL; RANCID BEEF 30 [hp_X]/1 mL; DELPHINIUM STAPHISAGRIA SEED 12 [hp_X]/1 mL; STAPHYLOCOCCUS EPIDERMIDIS 30 [hp_X]/1 mL; STAPHYLOCOCCUS HAEMOLYTICUS 30 [hp_X]/1 mL; STAPHYLOCOCCUS SIMULANS 30 [hp_X]/1 mL; STREPTOCOCCUS PYOGENES 30 [hp_X]/1 mL; SULFUR 30 [hp_X]/1 mL
INACTIVE INGREDIENTS: ALCOHOL; WATER

D-102

NDC 58264-0108-1

INDICATIONS

PURPOSE

Restoration of antibacterial system.

INGREDIENTS

ACTIVE

Allium sativum 12x, Aloe socotrina 6x, Bacillinum 30x, Eucalyptus globulus 12x, Lac caninum 30x, Lac vaccinum 30x, Pyrogenium 30x, Staphysagria 12x, 30x, Staphylococcinum 30x, Streptococcinum 30x, Sulphur 30x

INACTIVE

20% alcohol in purified water.

Rx CAUTION

Federal law prohibits dispensing without a prescription.

SUGGESTED DOSAGE

One dropper under tongue two times daily. Acute symptoms ½ dropper under tongue every 30 minutes for two hours.

STORAGE AND HANDLING

SHAKE WELL

Warnings

- Use only if cap seal is unbroken.

PREGNANCY OR BREAST FEEDING

- If pregnant or breastfeeding, ask a healthcare professional before use.

KEEP OUT OF REACH OF CHILDREN

- Keep this and all medication out of the reach of children.

To be used according to standard homeopathic indications.

PRINCIPAL DISPLAY PANEL - 1 FL. OZ. Bottle Label

DYNAMIC
NUTRITIONAL
ASSOCIATES, INC.

D 102

HOMEOPATHIC
STRESS FORMULA

1 FL. OZ.